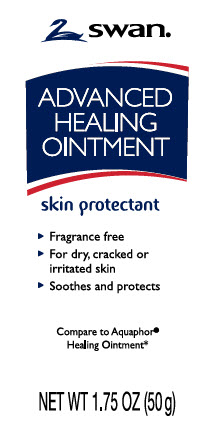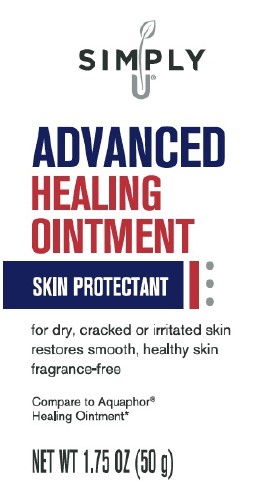 DRUG LABEL: Skin protectant
NDC: 11344-247 | Form: OINTMENT
Manufacturer: Consumer Product Partners, LLC
Category: otc | Type: HUMAN OTC DRUG LABEL
Date: 20250211

ACTIVE INGREDIENTS: PETROLATUM 410 mg/1 g
INACTIVE INGREDIENTS: MINERAL OIL; CERESIN; LANOLIN ALCOHOLS; PANTHENOL; GLYCERIN; LEVOMENOL

Swan_Simply U 247.000/247AC
Healing Ointment for Dry and Cracked Skin

Active ingredient

Petrolaturm 41%

Purpose

Skin protectant

Uses

- temporarily protects minor: cuts, scrapes, burns
- temporarily protects and helps relieve chapped and cracked skin and lips
- helps protect from the drying effects of wind and cold weather

Warnings

For external use only

Do not use on

- deep or puncture wounds
- animal bites
- serious burns

When using this product

- do not get in eyes

Stop use and ask a doctor if

- condition worsens
- symptoms last more than 7 days or clear up and occur again within a few days

Keep out of reach of children

If swallowed get medical help or contract a Poison Control Center right away

Directions

- apply as needed

Inactive ingredients

minerol oil, ceresin, lanolin alcohol, panthenol, glycerin, bisabolol

Questions?

Call 1-888-593-0593

Disclaimer

*This product is not manufactured or distributed by Beiersdorf Inc., distributor Aquaphor®Healing Ointment.

Adverse reactions

Distributed by:

Consumer Product Partners, LLC

St. Louis, MO, 63114

1-888-593-0593

Principal display panel

SWAN®

ADVANCED HEALING OINTMENT

skin protectant

- Fragrance free
- For dry, cracked or irritated skin
- Soothes and protects

Compare to Aquaphor®Healing Ointment*

NET WT 1.75 OZ (50 g)

PRINCIPAL DISPLAY PANEL

SIMPLY

U ®

ADVANCED

HEALING

OINTMENT

SKIN PROTECTANT

for dry, cracked or irritated skin

restores smooth, healthy skin

fragrance-free

Compare to Aquaphor ®

Healing Ointment*

NET WT 1.75 OZ (50 g)